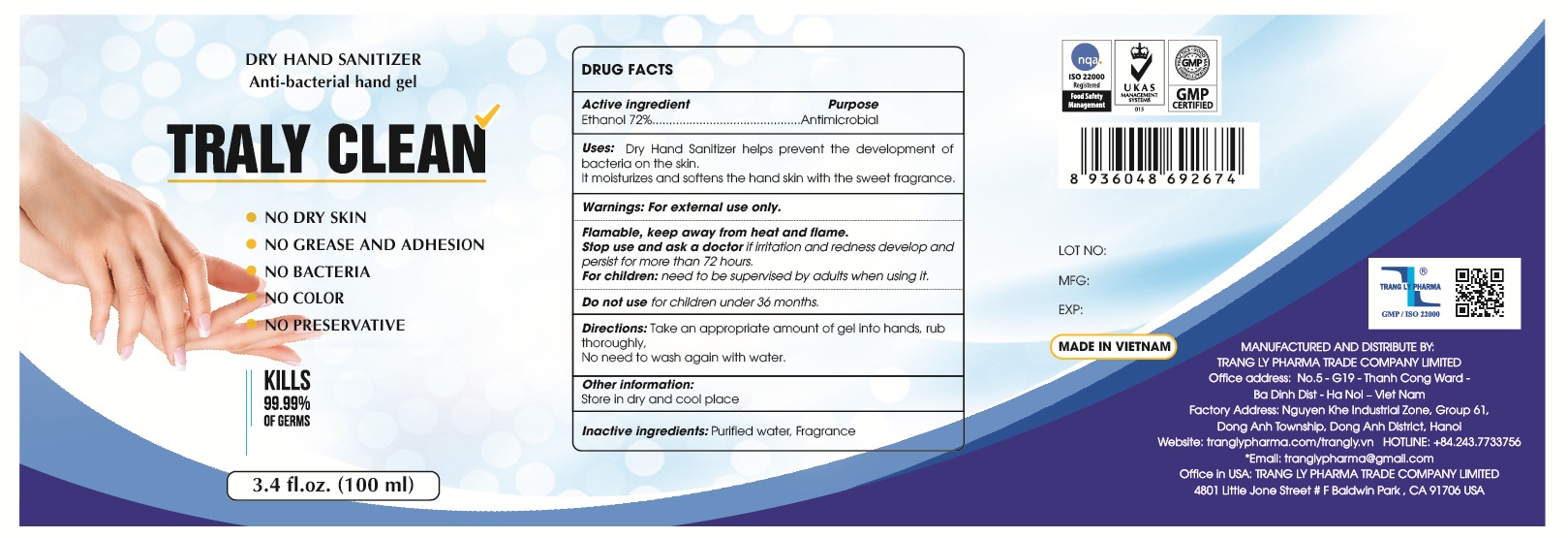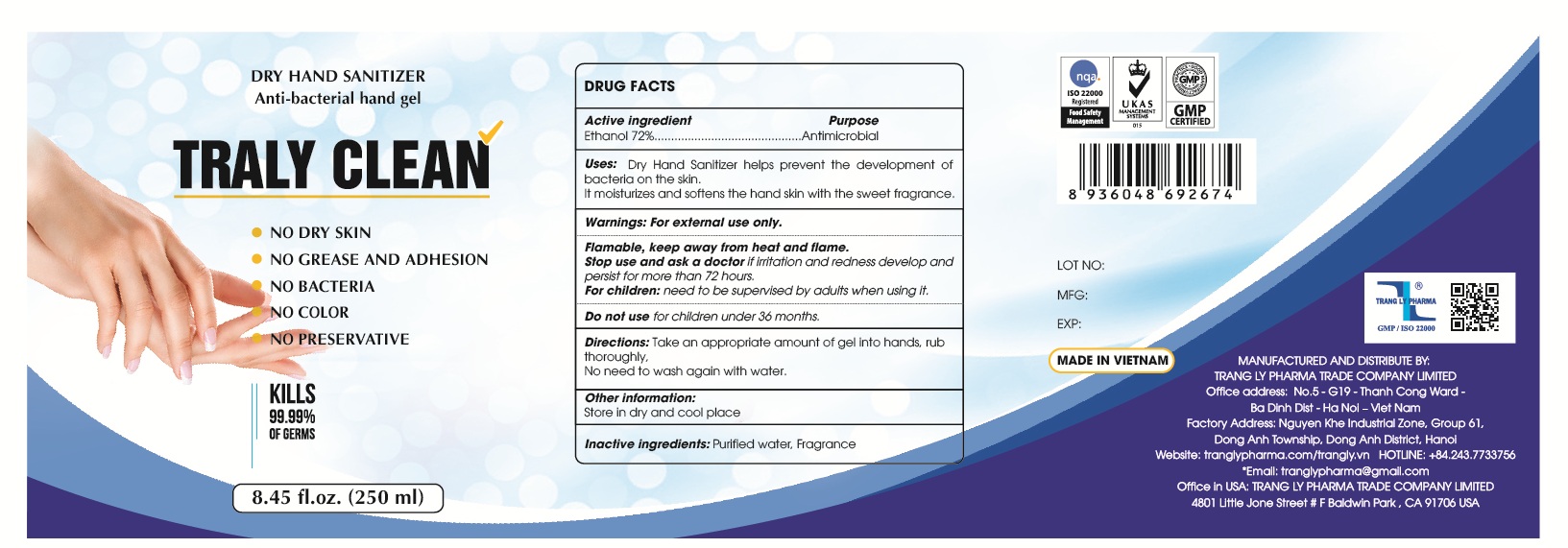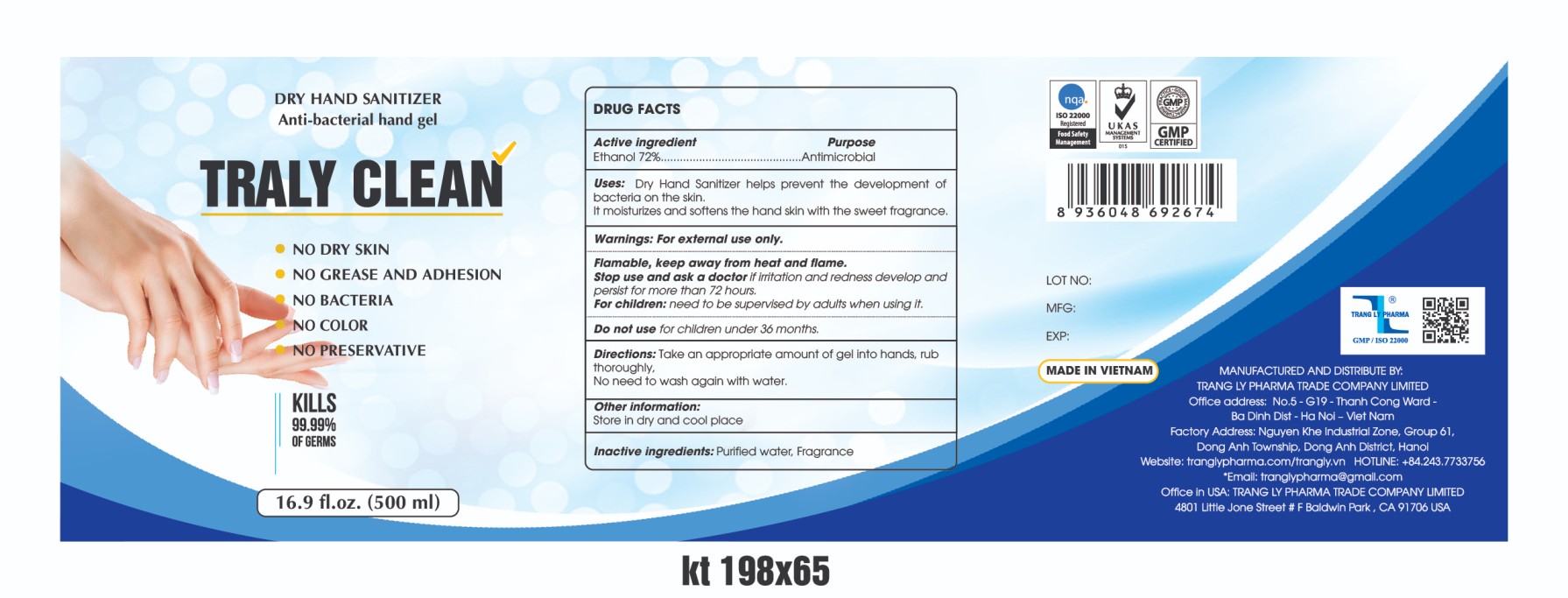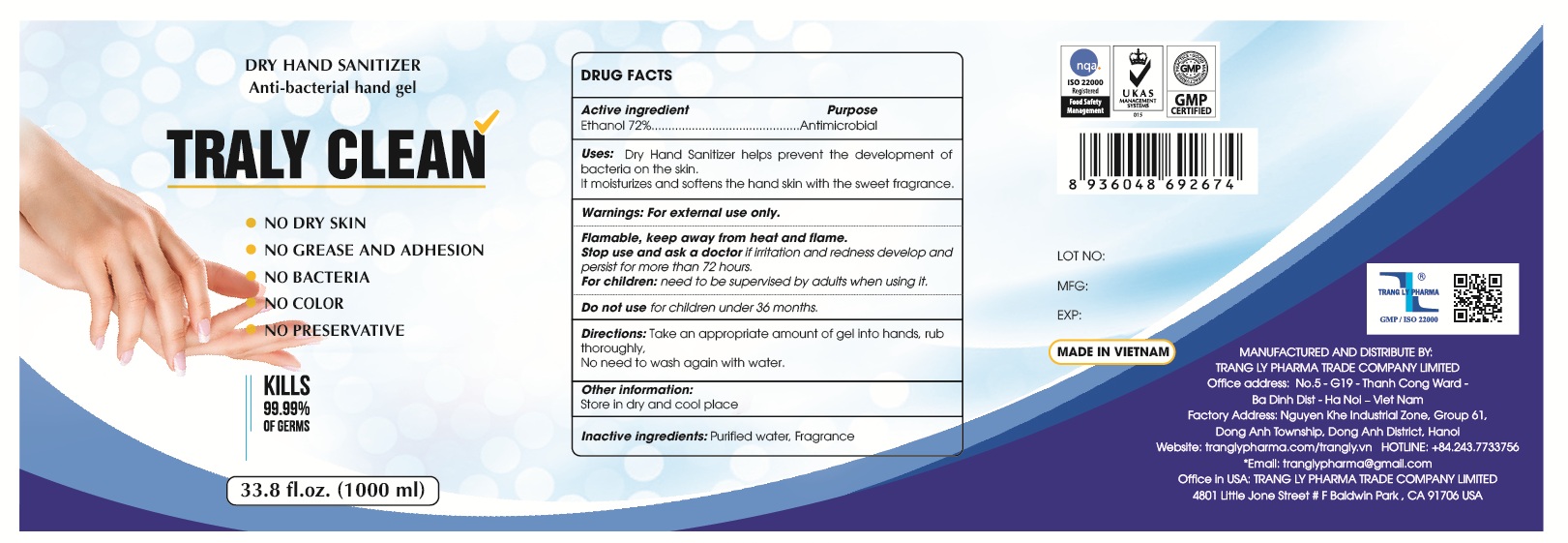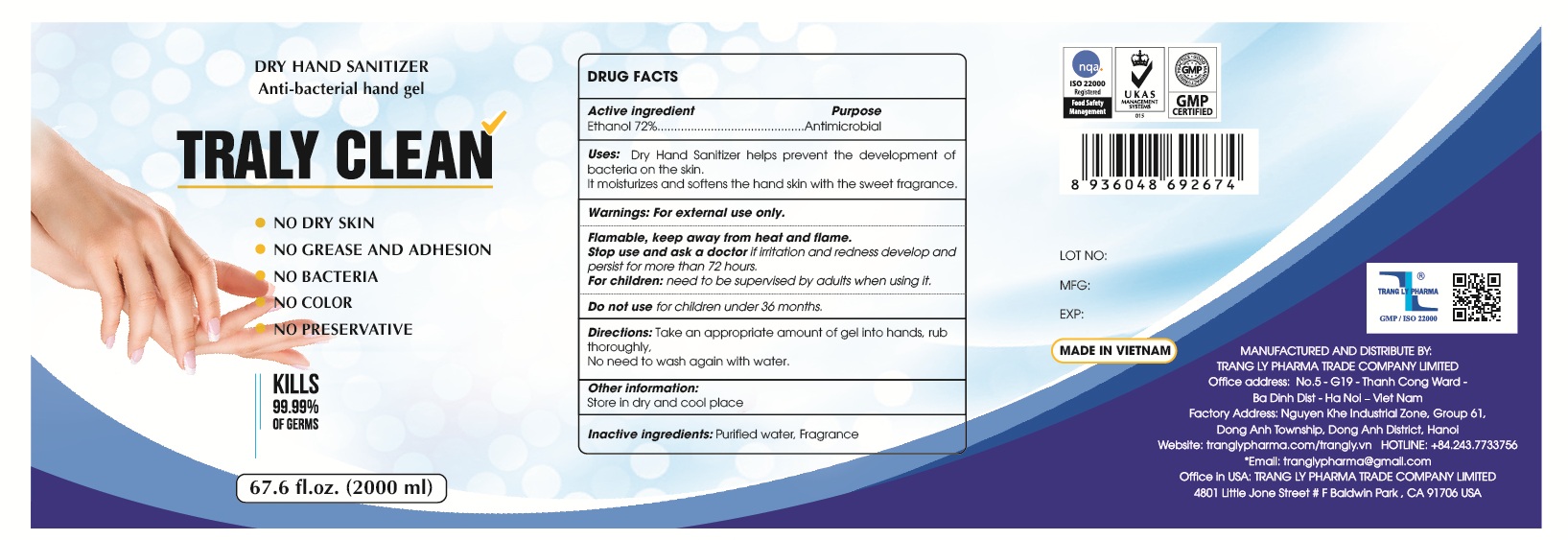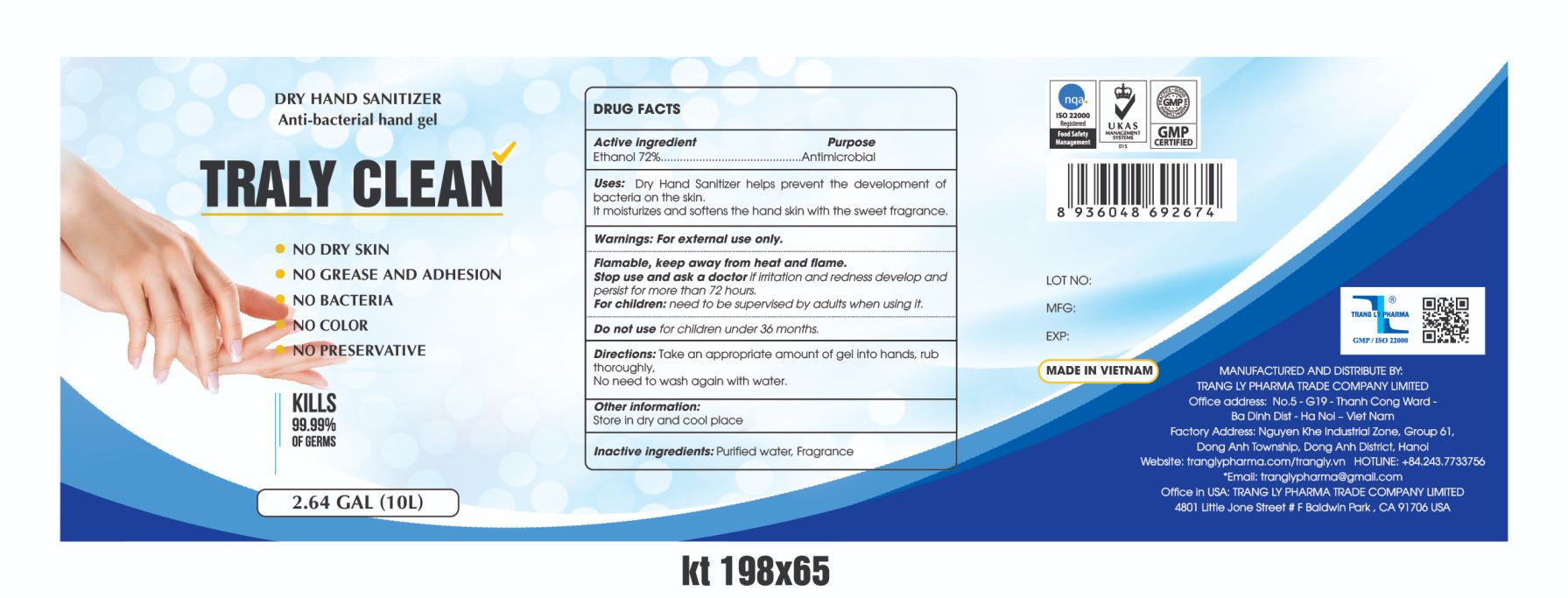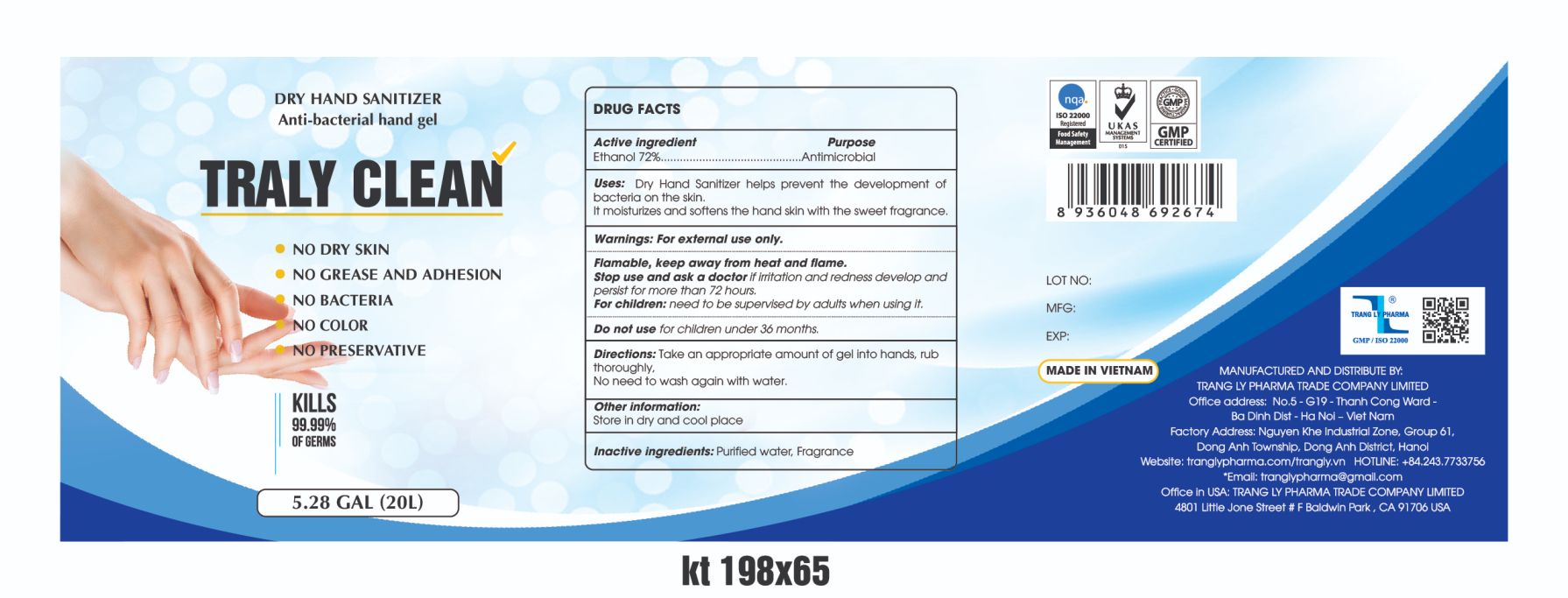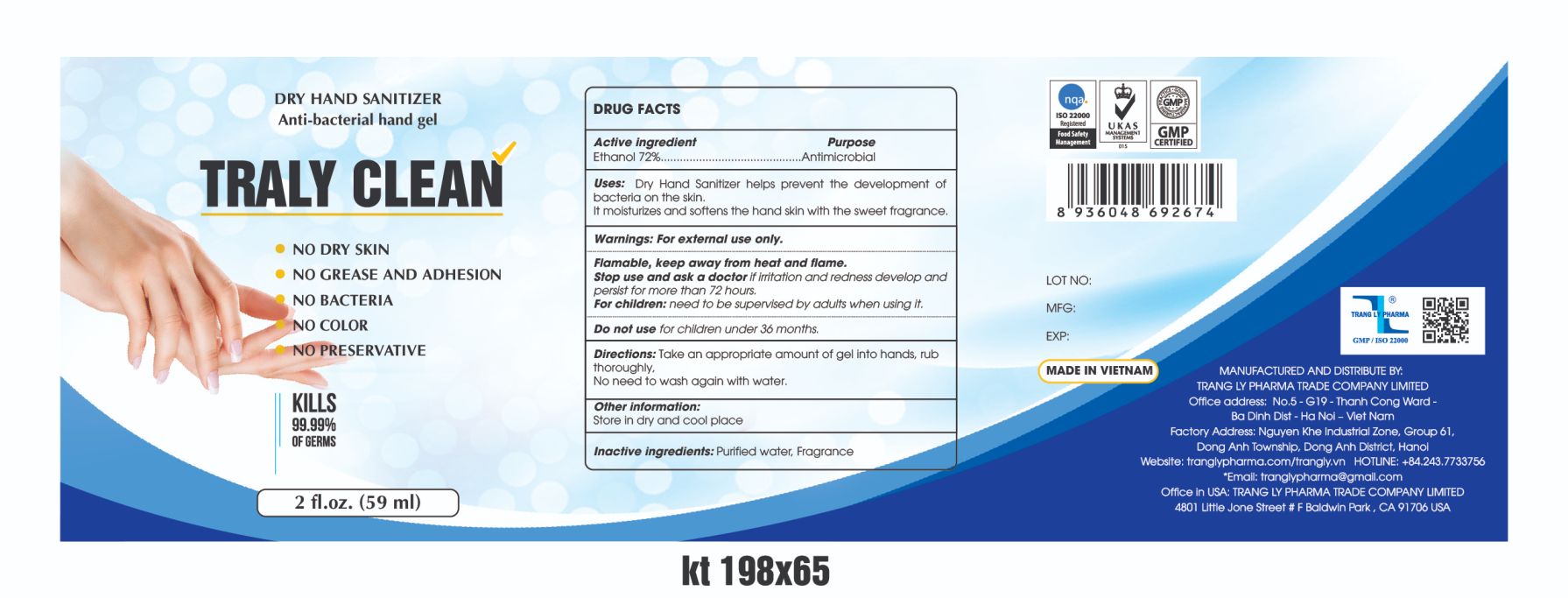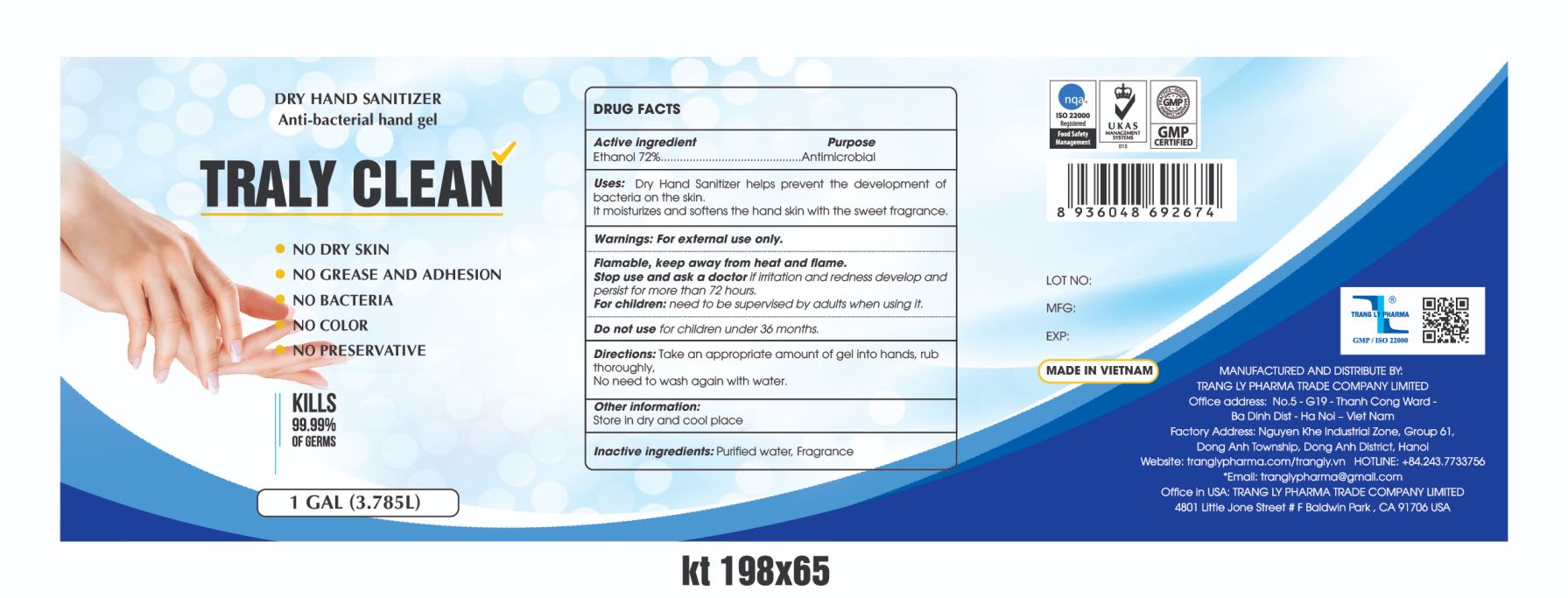 DRUG LABEL: Hand Sanitizer
NDC: 90098-100 | Form: GEL
Manufacturer: TRANG LY PHARMA TRADE COMPANY LIMITED
Category: otc | Type: HUMAN OTC DRUG LABEL
Date: 20201015

ACTIVE INGREDIENTS: ALCOHOL 72 mL/100 mL
INACTIVE INGREDIENTS: WATER 22 mL/100 mL; MINT 6 mL/100 mL

This is a hand sanitizer manufactured according to the Temporary Policy for Preparation of Certain Alcohol-Based Hand Sanitizer Products During the Public Health Emergency (CoViD-19); Guidance for Industry.

The hand sanitizer is manufactured using only the following United States Pharmacopoeia (USP) grade ingredients in the preparation of the product (percentage in final product formulation) consistent with World Health Organization (WHO) recommendations:

1. Alcohol (ethanol) (USP or Food Chemical Codex (FCC) grade) (80%, volume/volume (v/v)) in an aqueous solution denatured according to Alcohol and Tobacco Tax and Trade Bureau regulations in 27 CFR part 20.
2. Glycerol (1.45% v/v).
3. Hydrogen peroxide (0.125% v/v).
4. Sterile distilled water or boiled cold water.

The firm does not add other active or inactive ingredients. Different or additional ingredients may impact the quality and potency of the product.

Active Ingredient(s)

Alcohol 80% v/v. Purpose: Antiseptic

Purpose

Antimicrobial

Use

Dry Hand Sanitizer helps prevent the development of bacteria on the skin.

It moisturizes and softens the hand skin with the sweet fragrance.

Warnings

For external use only. Flammable. Keep away from heat or flame

Do not use

- for children under 36 months.

Stop use and ask a doctor if irritation and redness develop and persist for more than 72 hours.

For children: need to be supervised by adults when using it.

Stop use and ask a doctor if irritation or rash occurs. These may be signs of a serious condition.

Directions

- Place enough product on hands to cover all surfaces. Rub hands together until dry.
- Supervise children under 6 years of age when using this product to avoid swallowing.

Other information

- Store in dry and cool place

Inactive ingredients

glycerin, hydrogen peroxide, purified water USP

RECENT MAJOR CHANGES

Update Uses: from template to label description.

Keep our of reach of children

Package Label - Principal Display Panel

100 mL NDC: 90098-100-01

250 mL NDC: 90098-100-02

500 mL NDC: 90098-100-03

1000 mL NDC: 90098-100-04

2000 mL NDC: 90098-100-05

10000 mL NDC: 90098-100-06

20000 mL NDC: 90098-100-07

59 mL NDC: 90098-100-08

1 Gallon NDC: 90098-100-09